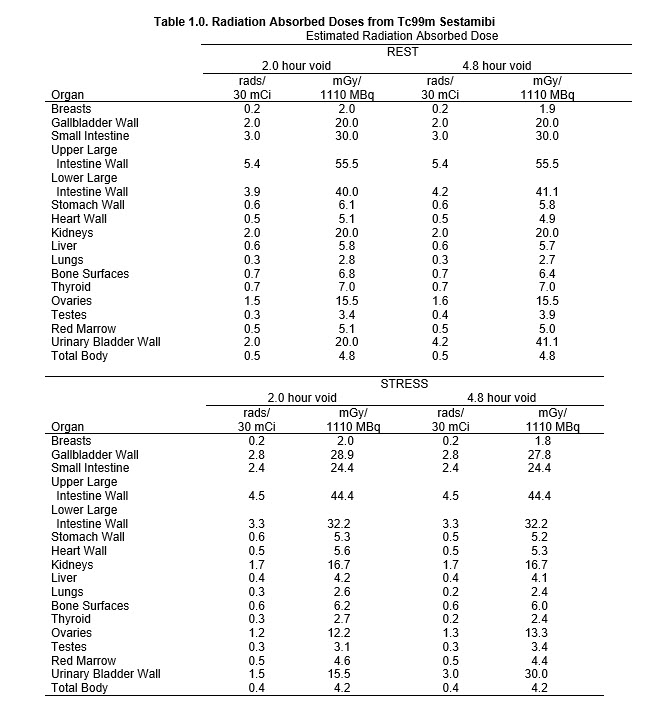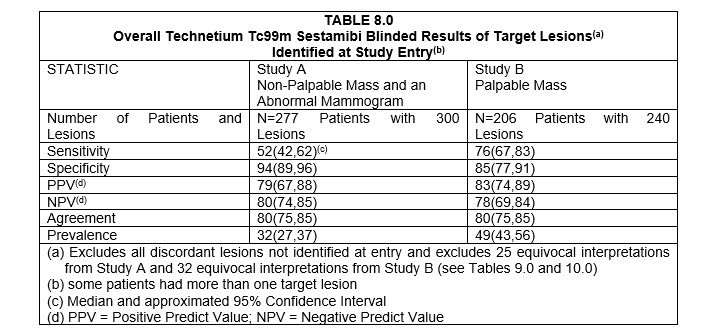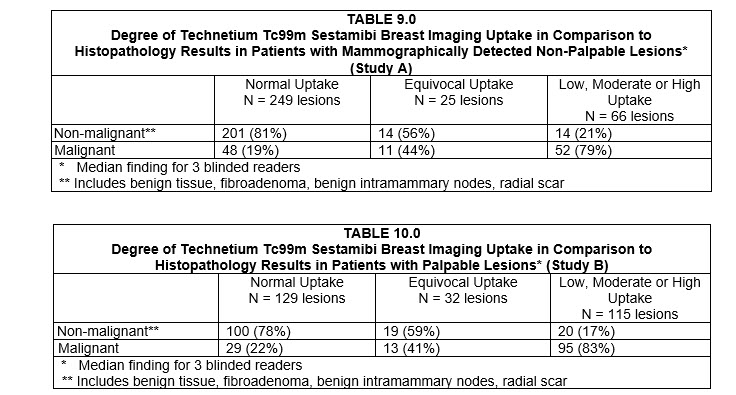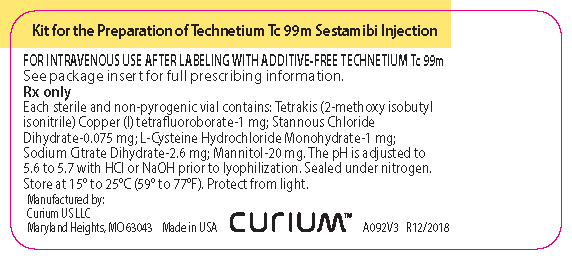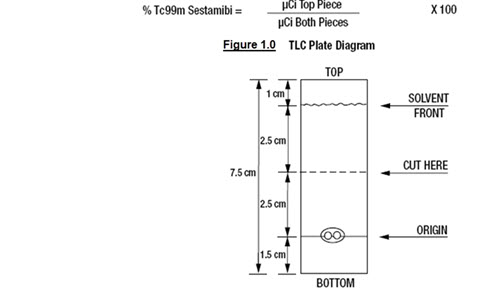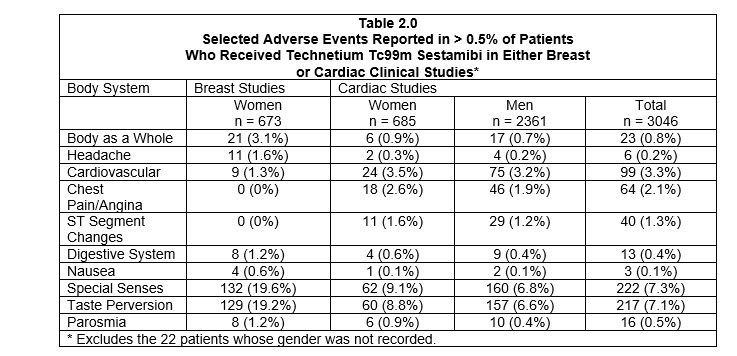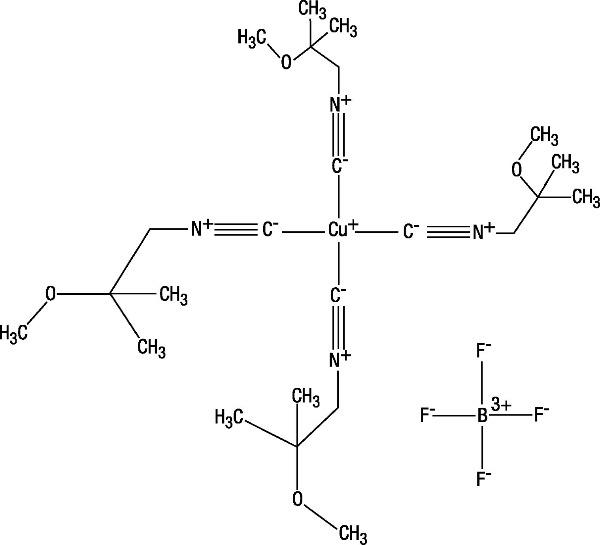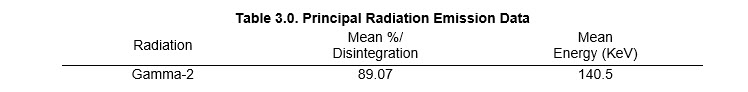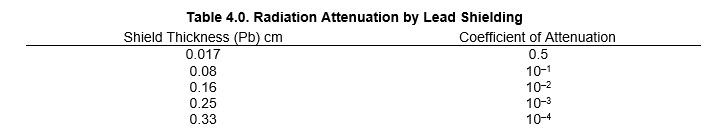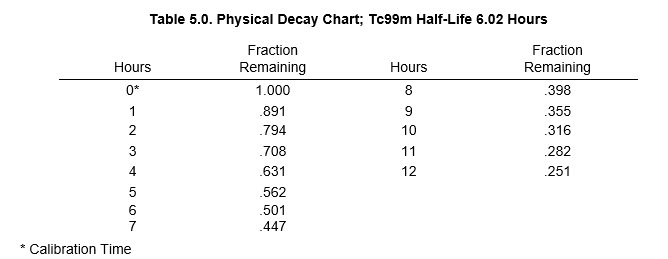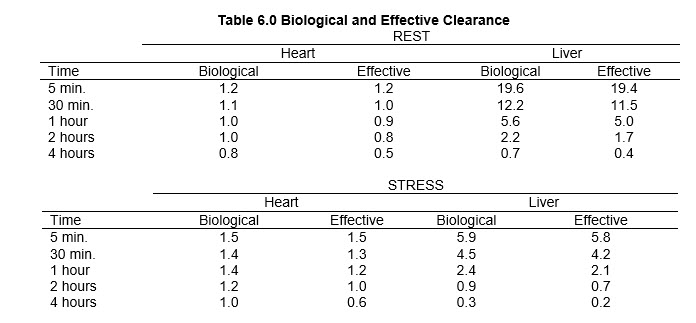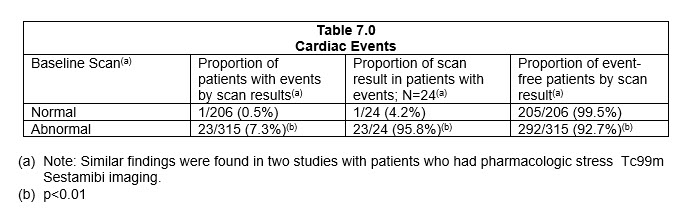 DRUG LABEL: Technetium Tc 99m Sestamibi
NDC: 69945-092 | Form: INJECTION
Manufacturer: Curium US LLC
Category: prescription | Type: HUMAN PRESCRIPTION DRUG LABEL
Date: 20220519

ACTIVE INGREDIENTS: TETRAKIS(2-METHOXYISOBUTYLISOCYANIDE)COPPER(I) TETRAFLUOROBORATE 1 mg/1 mL
INACTIVE INGREDIENTS: TRISODIUM CITRATE DIHYDRATE; CYSTEINE HYDROCHLORIDE; MANNITOL; STANNOUS CHLORIDE

HIGHLIGHTS OF PRESCRIBING INFORMATION

These highlights do not include all the information needed to use Kit for the Preparation of Technetium Tc99m Sestamibi Injection safely and effectively. See full prescribing information for Kit for the Preparation of Technetium Tc99m Sestamibi Injection.
Kit for the Preparation of Technetium Tc99m Sestamibi Injection
Initial U.S. Approval: December, 1990

1. INDICATIONS AND USAGE

Technetium Tc99m Sestamibi is a myocardial perfusion agent indicated for: (1)

- detecting coronary artery disease by localizing myocardial ischemia (reversible defects) and infarction (non-reversible defects)
- evaluating myocardial function and developing information for use in patient management decisions

2. DOSAGE AND ADMINISTRATION

- For Myocardial Imaging: The suggested dose range for I.V. administration of Technetium Tc99m Sestamibi in a single dose to be employed in the average patient (70 Kg) is 370-1110 MBq (10-30 mCi).
- For Breast Imaging: The recommended dose range for I.V. administration of Technetium Tc99m Sestamibi is a single dose of 740-1110 MBq (20-30 mCi).

3. DOSAGE FORMS AND STRENGTHS

Kit for the Preparation of Technetium Tc99m Sestamibi Injection is supplied as a lyophilized mixture in a 10 mL vial. (3)

4. CONTRAINDICATIONS

- None known.

5. WARNINGS AND PRECAUTIONS

- Pharmacologic induction of cardiovascular stress may be associated with serious adverse events such as myocardial infarction, arrhythmia, hypotension, bronchoconstriction and cerebrovascular events.
- Technetium Tc99m Sestamibi has been rarely associated with acute severe allergic and anaphylactic events of angioedema and generalized urticaria. In some patients the allergic symptoms developed on the second injection during Technetium Tc99m Sestamibi imaging.
- Caution should be exercised and emergency equipment should be available when administering Technetium Tc99m Sestamibi.
- Before administering Technetium Tc99m Sestamibi patients should be asked about the possibility of allergic reactions to either drug.
- The contents of the vial are intended only for use in the preparation of Technetium Tc99m Sestamibi and are not to be administered directly to the patient without first undergoing the preparative procedure.

6. ADVERSE REACTIONS

The following adverse reactions have been reported in ≤ 0.5% of patients: signs and symptoms consistent with seizure occurring shortly after administration of the agent; transient arthritis, angioedema, arrhythmia, dizziness, syncope, abdominal pain, vomiting, and severe hypersensitivity characterized by dyspnea, hypotension, bradycardia, asthenia, and vomiting within two hours after a second injection of Technetium Tc99m Sestamibi. A few cases of flushing, edema, injection site inflammation, dry mouth, fever, pruritis, rash, urticaria and fatigue have also been attributed to administration of the agent.

To report SUSPECTED ADVERSE REACTIONS, contact Curium US LLC at 1-866-789-2211 or FDA at 1-800-FDA-1088 or www.fda.gov/medwatch.

7. DRUG INTERACTIONS

- Specific drug-drug interactions have not been studied.

8. USE IN SPECIFIC POPULATIONS

- In one study of 46 subjects who received Technetium Tc99m Sestamibi administration, the radioactivity in both children and adolescents exhibited blood PK profiles similar to those previously reported in adults.
- Lactation: Interruption of breastfeeding after exposure to Technetium Tc99m Sestamibi is not necessary, however, a lactating woman should be advised to consider restricting close contact with her breast fed infant to a maximum of 5 hours in the 24 hour period after Technetium Tc99m Sestamibi administration in order to minimize radiation exposure. (8.2)

FULL PRESCRIBING INFORMATION

1. INDICATIONS AND USAGE

Myocardial Imaging: Kit for the Preparation of Technetium Tc99m Sestamibi Injection is a myocardial perfusion agent that is indicated for detecting coronary artery disease by localizing myocardial ischemia (reversible defects) and infarction (non-reversible defects), in evaluating myocardial function and developing information for use in patient management decisions. Technetium Tc99m Sestamibi evaluation of myocardial ischemia can be accomplished with rest and cardiovascular stress techniques (e.g., exercise or pharmacologic stress in accordance with the pharmacologic stress agent's labeling).

It is usually not possible to determine the age of a myocardial infarction or to differentiate a recent myocardial infarction from ischemia.

Breast Imaging: Kit for the Preparation of Technetium Tc99m Sestamibi Injection is indicated for planar imaging as a second line diagnostic drug after mammography to assist in the evaluation of breast lesions in patients with an abnormal mammogram or a palpable breast mass.

Kit for the Preparation of Technetium Tc99m Sestamibi Injection is not indicated for breast cancer screening, to confirm the presence or absence of malignancy, and it is not an alternative to biopsy.

2. DOSAGE AND ADMINISTRATION

For Myocardial Imaging: The suggested dose range for I.V. administration of Technetium Tc99m Sestamibi in a single dose to be employed in the average patient (70 Kg) is 370–1110 MBq (10–30 mCi).

For Breast Imaging: The recommended dose range for I.V. administration of Technetium Tc99m Sestamibi is a single dose of 740–1110 MBq (20–30 mCi).

2.1 Image Acquisition

Breast Imaging: It is recommended that images are obtained with a table overlay to separate breast tissue from the myocardium and liver, and to exclude potential activity that may be present in the opposite breast. For lateral images, position the patient prone with the isolateral arm comfortably above the head, shoulders flat against the table, head turned to the side and relaxed, with the breast imaged pendent through an overlay cutout. The breast should not be compressed on the overlay. For anterior images, position the patient supine with both arms behind the head. For either lateral or anterior images, shield the chest and abdominal organs, or remove them from the field of view.

For complete study, sets of images should be obtained five minutes after the injection, and in the following sequence:

Beginning five minutes after the injection of Technetium Tc99m Sestamibi:

- ten-minute lateral image of breast with abnormality
- ten-minute lateral image of contralateral breast
- ten-minute anterior image of both breasts

2.2 Radiation Dosimetry

The radiation doses to organs and tissues of an average patient (70 Kg) per 1110 MBq (30 mCi) of Technetium Tc99m Sestamibi injected intravenously are shown in Table 1.0.

Radiation dosimetry calculations performed by Radiation Internal Dose Information Center, Oak Ridge Institute for Science and Education, PO Box 117, Oak Ridge, TN 37831-0117.

2.3 Instructions For Preparation

Preparation of the Technetium Tc99m Sestamibi from the Kit for the Preparation of Technetium Tc99m Sestamibi is done by the following aseptic procedure:

General Procedure:

a. Prior to adding the Sodium Pertechnetate Tc99m Injection to the vial, inspect the vial carefully for the presence of damage, particularly cracks, and do not use the vial if found.
b. Waterproof gloves should be worn during the preparation procedure. Remove the plastic disc from the vial and swab the top of the vial closure with alcohol to sanitize the surface.

Boiling Water Bath Procedure:

c. Place the vial in a suitable radiation shield with a fitted radiation cap.
d. With a sterile shielded syringe, aseptically obtain additive-free, sterile, non-pyrogenic Sodium Pertechnetate Tc99m Injection [925-5550 MBq, (25-150 mCi)] in approximately 1 to 3 mL.
e. Aseptically add the Sodium Pertechnetate Tc99m Injection to the vial in the lead shield. Without withdrawing the needle, remove an equal volume of headspace to maintain atmospheric pressure within the vial.
f. Shake vigorously, about 5 to 10 quick upward-downward motions.
g. Remove the vial from the lead shield and place upright in an appropriately shielded and contained boiling water bath, such that the vial is suspended above the bottom of the bath, and boil for 10 minutes. Timing for 10 minutes is begun as soon as the water begins to boil again. Do not allow the boiling water to come in contact with the aluminum crimp.
h. Remove the vial from the water bath, place in the lead shield and allow to cool for fifteen minutes.
i. Using proper shielding, the vial contents should be visually inspected. Use only if the solution is clear and free of particulate matter and discoloration.
j. Assay the reaction vial using a suitable radioactivity calibration system. Record the Technetium Tc99m concentration, total volume, assay time and date, expiration time and lot number on the radioassay information label and affix the label to the shield.
k. Store the reaction vial containing the Technetium Tc99m Sestamibi at 15° to 25°C (59° - 77°F) until use; at such time the product should be aseptically withdrawn. Technetium Tc99m Sestamibi should be used within six hours of preparation. The vial contains no preservative.

Note: Adherence to the above product reconstitution instructions is recommended.

Curium US LLC’s Kit for the Preparation of Technetium Tc99m Sestamibi Injection is not to be used with the Recon-o-Stat™ thermal cycler due to the smaller vial size requirements of this heating device.

The potential for cracking and significant contamination exists whenever vials containing radioactive material are heated.

Product should be used within 6 hours after preparation.

Final product with radiochemical purity of at least 90% was used in the clinical trials that established safety and effectiveness. The radiochemical purity was determined by the following method.

2.4 Determination of Radiochemical Purity in Technetium Tc99m Sestamibi

1. Obtain a Baker-Flex Aluminum Oxide coated, plastic TLC plate, #1 B-F, pre-cut to 2.5 cm x 7.5 cm.
2. Dry the plate or plates at 100°C for 1 hour and store in a desiccator. Remove pre-dried plate from the desiccator just prior to use.
3. Apply 1 drop of ethanol* using a 1 mL syringe with a 22-26 gauge needle, 1.5 cm from the bottom of the plate. THE SPOT SHOULD NOT BE ALLOWED TO DRY.
4. Add 2 drops of Technetium Tc99m Sestamibi solution, side by side on top of the ethanol* spot. Return the plate to a desiccator and allow the sample spot to dry (typically 15 minutes).
5. The TLC tank is prepared by pouring ethanol* to a depth of 3-4 mm. Cover the tank and let it equilibrate for ~10 minutes.
6. Develop the plate in the covered TLC tank in ethanol* for a distance of 5 cm from the point of application.
7. Cut the TLC plate 4 cm from the bottom and measure the Tc99m activity in each piece by appropriate radiation detector.
8. Calculate the % Tc99m Sestamibi as:

*The ethanol used in this procedure should be 95% or greater. Absolute ethanol (99%) should remain at ≥95% ethanol content for one week after opening if stored tightly capped, in a cool dry place.

3. DOSAGE FORMS AND STRENGTHS

Kit for the Preparation of Technetium Tc99m Sestamibi Injection is supplied as a lyophilized mixture in a 10 mL vial.

4. CONTRAINDICATIONS

None known.

5. WARNINGS AND PRECAUTIONS

5.1 Warnings

In studying patients in whom cardiac disease is known or suspected, care should be taken to assure continuous monitoring and treatment in accordance with safe, accepted clinical procedure. Infrequently, death has occurred 4 to 24 hours after Tc99m Sestamibi use and is usually associated with exercise stress testing (See Section 5.2).

Pharmacologic induction of cardiovascular stress may be associated with serious adverse events such as myocardial infarction, arrhythmia, hypotension, bronchoconstriction and cerebrovascular events. Caution should be used when pharmacologic stress is selected as an alternative to exercise; it should be used when indicated and in accordance with the pharmacologic stress agent's labeling.

Technetium Tc99m Sestamibi has been rarely associated with acute severe allergic and anaphylactic events of angioedema and generalized urticaria. In some patients the allergic symptoms developed on the second injection during Tc99m Sestamibi imaging. Patients who receive Technetium Tc99m Sestamibi for either myocardial or breast imaging are receiving the same drug. Caution should be exercised and emergency equipment should be available when administering Technetium Tc99m Sestamibi. Also, before administering Technetium Tc99m Sestamibi Injection, patients should be asked about the possibility of allergic reactions to the drug.

5.2 General Precautions

The contents of the vial are intended only for use in the preparation of Technetium Tc99m Sestamibi and are not to be administered directly to the patient without first undergoing the preparative procedure.

Radioactive drugs must be handled with care and appropriate safety measures should be used to minimize radiation exposure to clinical personnel. Also, care should be taken to minimize radiation exposure to the patients consistent with proper patient management.

Contents of the kit before preparation are not radioactive. However, after the Sodium Pertechnetate Tc99m Injection is added, adequate shielding of the final preparation must be maintained. The components of the kit are sterile and non-pyrogenic. It is essential to follow directions carefully and to adhere to strict aseptic procedures during preparation.

Technetium Tc99m labeling reactions depend on maintaining the stannous ion in the reduced state. Hence, Sodium Pertechnetate Tc99m Injection containing oxidants should not be used.

Technetium Tc99m Sestamibi should not be used more than six hours after preparation.

Radiopharmaceuticals should be used only by physicians who are qualified by training and experience in the safe use and handling of radionuclides and whose experience and training have been approved by the appropriate government agency authorized to license the use of radionuclides.

Stress testing should be performed only under the supervision of a qualified physician and in a laboratory equipped with appropriate resuscitation and support apparatus.

The most frequent exercise stress test endpoints sufficient to stop the test reported during controlled studies (two-thirds were cardiac patients) were:

Fatigue 35%
Dyspnea 17%
Chest Pain 16%
ST-depression 7%
Arrhythmia 1%

6. ADVERSE REACTIONS

Adverse events were evaluated in 3741 adults who were evaluated in clinical studies. Of these patients, 3068 (77% men, 22% women, and 0.7% of the patients' genders were not recorded) were in cardiac clinical trials and 673 (100% women) in breast imaging trials. Cases of angina, chest pain, and death have occurred (see Section 5). Adverse events reported at a rate of 0.5% or greater after receiving Technetium Tc99m Sestamibi administration are shown in the following table:

In the clinical studies for breast imaging, breast pain was reported in 12 (1.7%) of the patients. In 11 of these patients the pain appears to be associated with biopsy/surgical procedures.

The following adverse reactions have been reported in ≤ 0.5% of patients: signs and symptoms consistent with seizure occurring shortly after administration of the agent; transient arthritis; angioedema, arrhythmia, dizziness, syncope, abdominal pain, vomiting, and severe hypersensitivity characterized by dyspnea, hypotension, bradycardia, asthenia, and vomiting within two hours after a second injection of Technetium Tc99m Sestamibi. A few cases of flushing, edema, injection site inflammation, dry mouth, fever, pruritus, rash, urticaria and fatigue have also been attributed to administration of the agent.

7. DRUG INTERACTIONS

Specific drug-drug interactions have not been studied.

8. USE IN SPECIFIC POPULATIONS

8.1 Pregnancy

Risk Summary
Limited available data with Technetium Tc99m Sestamibi use in pregnant women have not identified a drug-associated risk of major birth defects, miscarriage, or adverse maternal or fetal outcomes. Animal reproduction and teratogenicity studies have not been conducted with Technetium Tc99m Sestamibi. However, all radiopharmaceuticals have the potential to cause fetal harm depending on the fetal stage of development and the magnitude of the radiation dose. If considering Technetium Tc99m Sestamibi administration to a pregnant woman, inform the patient about the potential for adverse pregnancy outcomes based on the radiation dose from Technetium Tc99m Sestamibi and the gestational timing of exposure.

All pregnancies have a background risk of birth defects, loss, or other adverse outcomes. In the U.S. general population, the estimated background risk of major birth defects and miscarriage in clinically recognized pregnancies is 2-4% and 15-20%, respectively.

8.2 Lactation

Risk Summary
Limited data in the scientific literature on the presence of Technetium Tc99m Sestamibi in human milk, demonstrate that between 0.01% and 0.03% of maternal injected activity of Technetium Tc99m Sestamibi was excreted in human milk. Technetium Tc99m Sestamibi accumulates in the lactating breast [see Clinical Considerations]. There are limited data in the scientific literature on effects of Technetium Tc99m Sestamibi on breastfed infant or on milk production. The developmental and health benefits of breastfeeding should be considered along with the mother’s clinical need for Technetium Tc99m Sestamibi and any potential adverse effects on the breastfed infant from Technetium Tc99m Sestamibi or from the underlying maternal condition.

Clinical Considerations
Interruption of breastfeeding after exposure to Technetium Tc99m Sestamibi is not necessary because Technetium Tc99m Sestamibi excretion in breast milk is low. However, a lactating woman may restrict close contact with her breast fed infant to a maximum of 5 hours in the 24 hour period after Technetium Tc99m Sestamibi administration in order to minimize radiation exposure.

8.4 Pediatric Use

Safety and effectiveness in the pediatric population have not been established.

No evidence of diagnostic efficacy or clinical utility of Technetium Tc99m Sestamibi scan was found in clinical studies of children and adolescents with Kawasaki disease.

A prospective study of 445 pediatric patients with Kawasaki disease was designed to determine the predictive value of Technetium Tc99m Sestamibi rest and stress myocardial perfusion imaging to define a pediatric population with Kawasaki disease that was at risk of developing cardiac events. Cardiac events were defined as cardiac death, MI, hospitalization due to cardiac etiology, heart failure, CABG or coronary angioplasty. The standard of truth was defined as cardiac events occurring 6 months following the administration of Technetium Tc99m Sestamibi. Only three cardiac events were observed at six months in this study. In all three cases, the scan was negative. No clinically meaningful measurements of sensitivity, specificity or other diagnostic performance parameters could be demonstrated in this study.

A ten year retrospective case history study of pediatric Kawasaki disease patients who completed Technetium Tc99m Sestamibi myocardial perfusion imaging and who had coronary angiography within three months of the Technetium Tc99m Sestamibi scan was designed to measure sensitivity and specificity of Technetium Tc99m Sestamibi scan. Out of 72 patients who had both evaluable Technetium Tc99m Sestamibi scans and evaluable angiographic images, only one patient had both an abnormal angiogram and an abnormal Technetium Tc99m Sestamibi scan. No clinically meaningful measurements of sensitivity, specificity or other diagnostic performance parameters could be demonstrated in this study.

In a clinical pharmacology study, 46 pediatric patients with Kawasaki disease received Technetium Tc99m Sestamibi administration at the following doses: 0.1-0.2 mCi/kg for rest, 0.3 mCi/kg for stress in one day studies; 0.2 mCi/kg for rest and 0.2 mCi/kg for stress in two day studies.

The radioactivity both in younger children and in adolescents exhibited PK profiles similar to those previously reported in adults (See Section 12).

The radiation absorbed doses in adolescents, both at rest and stress, were similar to those observed in adults (see Section 2). When comparing weight-adjusted radioactivity (up to 0.3 mCi/kg) doses administered to adolescents and younger children to the recommended dose administered to adults (up to 30 mCi), the radiation absorbed doses in both adolescents and younger children were similar to those in adults.

Adverse events were evaluated in 609 pediatric patients from the three clinical studies described above. The frequency and the type of the adverse events were similar to the ones observed in the studies of Technetium Tc99m Sestamibi in adults. Two of the 609 had a serious adverse event: one patient received a Technetium Tc99m Sestamibi overdose but remained asymptomatic, and one patient had an asthma exacerbation following administration.

8.5 Geriatric Use

Of 3068 patients in clinical studies of Technetium Tc99m Sestamibi for myocardial imaging, 693 patients were 65 or older and 121 were 75 or older.

Of 673 patients in clinical studies of Technetium Tc99m Sestamibi for breast imaging, 138 patients were 65 or older and 30 were 75 or older.

Based on the evaluation of the frequency of adverse events and review of vital signs data, no overall differences in safety were observed between these subjects and younger subjects. Although reported clinical experience has not identified differences in response between elderly and younger patients, greater sensitivity of some older individuals cannot be ruled out.

10. OVERDOSAGE

The clinical consequences of overdosing with Technetium Tc99m Sestamibi are not known.

11. DESCRIPTION

Each 10 mL vial contains a sterile, non-pyrogenic, lyophilized mixture of:

- Tetrakis (2-methoxy isobutyl isonitrile) Copper (I) tetrafluoroborate – 1 mg
- Sodium Citrate Dihydrate - 2.6 mg
- L-Cysteine Hydrochloride Monohydrate – 1 mg
- Mannitol - 20 mg
- Stannous Chloride, Dihydrate, minimum (SnCl2•2H2O) - 0.025 mg
- Stannous Chloride, Dihydrate (SnCl2•2H2O) - 0.075 mg
- Tin Chloride (stannous and stannic) Dihydrate, maximum (as SnCl2•2H2O) -
  0.086 mg

Prior to lyophilization the pH is 5.6 to 5.7, and sodium hydroxide and/or hydrochloric acid may have been added for pH adjustment. The contents of the vial are lyophilized and stored under nitrogen.

This drug is administered by intravenous injection for diagnostic use after reconstitution with sterile, non-pyrogenic, oxidant-free Sodium Pertechnetate Tc99m Injection. The pH of the reconstituted product is 5.5 (5.0-6.0). No bacteriostatic preservative is present.

The precise structure of the technetium complex is Tc99m[MIBI]6+ where MIBI is 2-methoxy isobutyl isonitrile.

Tetrakis (2-methoxy isobutyl isonitrile) Copper (I) tetrafluoroborate has the following structural formula:

Structural formula

The molecular formula is C24H44N4O4BF4Cu, and the molecular weight is 602.98.

11.1 Physical Characteristics

Technetium Tc99m decays by isomeric transition with a physical half-life of 6.02 hours.^1 Photons that are useful for detection and imaging studies are listed below in Table 3.0.

^1 Kocher, David, C., Radioactive Decay Data Tables, DOE/TIC-11026, 108(1981).

11.2 External Radiation

The specific gamma ray constant for Tc99m is 5.4 microcoulombs/Kg-MBq-hr (0.78 R/mCi-hr) at 1 cm. The first half value layer is 0.017 cm of Pb. A range of values for the relative attenuation of the radiation emitted by this radionuclide that results from interposition of various thicknesses of Pb is shown in Table 4.0. To facilitate control of the radiation exposure from Megabequerel (millicurie) amounts of this radionuclide, the use of a 0.25 cm thickness of Pb will attenuate the radiation emitted by a factor of 1,000.

To correct for physical decay of this radionuclide, the fractions that remain at selected intervals after the time of calibration are shown in Table 5.0.

12. CLINICAL PHARMACOLOGY

12.1 Mechanism of Action

Technetium Tc99m Sestamibi is a cationic Tc99m complex which has been found to accumulate in viable myocardial tissue in a manner analogous to that of thallous chloride Tl-201. Scintigraphic images obtained in humans after the intravenous administration of the drug have been comparable to those obtained with thallous chloride Tl-201 in normal and abnormal myocardial tissue.

Animal studies have shown that myocardial uptake is not blocked when the sodium pump mechanism is inhibited. Although studies of subcellular fractionation and electron micrographic analysis of heart cell aggregates suggest that Tc99m Sestamibi cellular retention occurs specifically within the mitochondria as a result of electrostatic interactions, the clinical relevance of these findings has not been determined.

The mechanism of Tc99m Sestamibi localization in various types of breast tissue (e.g., benign, inflammatory, malignant, fibrous) has not been established.

12.3 Pharmacokinetics

Pulmonary activity is negligible even immediately after injection. Blood clearance studies indicate that the fast clearing component clears with a t½ of 4.3 minutes at rest, and clears with a t½ of 1.6 minutes under exercise conditions. At five minutes post injection about 8% of the injected dose remains in circulation. There is less than 1% protein binding of Technetium Tc99m Sestamibi in plasma. The myocardial biological half-life is approximately six hours after a rest or exercise injection. The biological half-life for the liver is approximately 30 minutes after a rest or exercise injection. The effective half-life of clearance (which includes both the biological half-life and radionuclide decay) for the heart is approximately 3 hours, and for the liver is approximately 30 minutes, after a rest or exercise injection. The ideal imaging time reflects the best compromise between heart count rate and surrounding organ uptake.

Myocardial uptake which is coronary flow dependent is 1.2% of the injected dose at rest and 1.5% of the injected dose at exercise. Table 6.0 illustrates the biological clearance as well as effective clearance (which includes biological clearance and radionuclide decay) of Tc99m Sestamibi from the heart and liver.

[Organ concentrations expressed as percentage of injected dose; data based on an average of 5 subjects at rest and 5 subjects during exercise].

A study in a dog myocardial ischemia model reported that Technetium Tc99m Sestamibi undergoes myocardial distribution (redistribution), although more slowly and less completely than thallous chloride Tl-201. A study in a dog myocardial infarction model reported that the drug showed no redistribution of any consequence. Definitive human studies to demonstrate possible redistribution have not been reported. In patients with documented myocardial infarction, imaging revealed the infarct up to four hours post dose.

12.3.1 Metabolism

The agent is excreted without any evidence of metabolism.

12.3.2 Elimination

The major pathway for clearance of Tc99m Sestamibi is the hepatobiliary system. Activity from the gall bladder appears in the intestines within one hour of injection. Twenty-seven percent of the injected dose is excreted in the urine, and approximately thirty-three percent of the injected dose is cleared through the feces in 48 hours.

13. NONCLINICAL TOXICOLOGY

13.1 Carcinogenesis, Mutagenesis, Impairment of Fertility

In comparison with most other diagnostic technetium labeled radiopharmaceuticals, the radiation dose to the ovaries (1.5 rads/30 mCi at rest, 1.2 rads/30 mCi at exercise) is high. Minimal exposure (ALARA) is necessary in women of childbearing capability. (See Section 2.)

The active intermediate, Cu(MIBI)4BF4, was evaluated for genotoxic potential in a battery of five tests. No genotoxic activity was observed in the Ames, CHO/HPRT and sister chromatid exchange tests (all in vitro). At cytotoxic concentrations (>20 µg/mL), an increase in cells with chromosome aberrations was observed in the in vitro human lymphocyte assay. Cu(MIBI)4BF4 did not show genotoxic effects in the in vivo mouse micronucleus test at a dose which caused systemic and bone marrow toxicity (9 mg/kg, > 600 X maximal human dose).

14. CLINICAL STUDIES

CLINICAL TRIALS:

MYOCARDIAL IMAGING: In a trial of rest and stress Tc99m Sestamibi imaging, the relationship of normal or abnormal perfusion scans and long term cardiac events was evaluated in 521 patients (511 men, 10 women) with stable chest pain. There were 73.9% Caucasians, 25.9% Blacks and 0.2% Asians. The mean age was 59.6 years (range: 29 to 84 years). All patients had a baseline rest and exercise Tc99m Sestamibi scan and were followed for 13.2 ± 4.9 months (range: 1 to 24 months). Images were correlated with the occurrence of a cardiac event (cardiac death or non-fatal myocardial infarction). In this trial as summarized in Table 7.0, 24/521 (4.6%) had a cardiac event.

Although patients with normal images had a lower cardiac event rate than those with abnormal images, in all patients with abnormal images it was not possible to predict which patient would be likely to have further cardiac events; i.e., such individuals were not distinguishable from other patients with abnormal images.

The findings were not evaluated for defect location, disease duration, specific vessel involvement or intervening management.

In earlier trials, using a template consisting of the anterior wall, inferior-posterior wall and isolated apex, localization in the anterior or inferior-posterior wall in patients with suspected angina or coronary artery disease was shown. Disease localization isolated to the apex has not been established. In adults, Tc99m Sestamibi has not been studied or evaluated in cardiac disorders other than coronary artery disease.

BREAST IMAGING: Technetium Tc99m Sestamibi was evaluated in two multicenter, clinical trials of a total of 673 woman patients. Overall the mean age was 52 (range 23 to 87 years). The racial and ethnic representation was 70% Caucasian, 15% African-American, 14% Hispanic and 1% Asian.

Both clinical studies evaluated women who were referred for further evaluation for either: 1) a mammographically detected (with varying degrees of malignant likelihood) but not palpable breast lesion (study A, n=387, mean age = 54 years), or 2) a palpable breast lesion (study B, n=286, mean age = 50 years). In both studies all patients were scheduled for biopsy.

Technetium Tc99m Sestamibi (20-30 mCi) was injected intravenously in a vein that was contralateral to the breast lesion in question. Planar imaging was completed with a high resolution collimator with a 10% window centered at 140 KeV, and 128 x 128 matrix. An initial marker image, that was not used in the data analysis, was obtained using a cobalt Co57 point source as a marker of a palpable mass. Images were obtained 5 minutes after injection as follows: lateral image of the affected breast for 10 minutes, lateral image of the contralateral breast for 10 minutes, and an anterior image of both breasts for 10 minutes. For the lateral image the patients were positioned in a prone position. For the anterior image, the patients were supine. The Technetium Tc99m Sestamibi scintigraphic images were read in a randomized method by two groups of three blinded readers. Technetium Tc99m Sestamibi uptake was scored as: normal (no uptake), equivocal, low, moderate, or high uptake. The results of Technetium Tc99m Sestamibi images and mammography were analyzed in comparison to histopathologic findings of malignant or non-malignant disease.

As shown in Table 8.0 for the 483 evaluable patients, the sensitivity and specificity of any degree of Technetium Tc99m Sestamibi uptake appear to vary with the presence or absence of palpable mass.

In separate retrospective subset analyses of 259 patients with dense (heterogeneously/extremely dense) and 275 patients with fatty (almost entirely fat/numerous vague densities) breast tissue, the Technetium Tc99m Sestamibi results were similar. Overall, the studies were not designed to compare the performance of Technetium Tc99m Sestamibi with the performance of mammography in patients with breast densities or other coexistent breast tissue disorders.

In general the histology seems to correlate with the degree of Technetium Tc99m Sestamibi uptake. As shown in Tables 9.0 and 10.0, the majority of the normal Technetium Tc99m Sestamibi images are associated with non-malignant tissue (78-81%) and the majority of low, moderate or high uptake Technetium Tc99m Sestamibi images are associated with malignant disease (79-83%). In an individual patient, however, the intensity of Technetium Tc99m Sestamibi uptake can not be used to confirm the presence or absence of malignancy. Equivocal results do not have a correlation with histology.

An estimate of the likelihood of malignancy based on the Technetium Tc99m Sestamibi uptake score in combination with the mammographic score has not been studied.

In these two studies approximately 150 additional, non-biopsied lesions were found to be positive after Technetium Tc99m Sestamibi imaging. These lesions were identified in sites that did not physically correlate with identified entry criteria mammographic lesions and these lesions were not palpable. These lesions were not biopsied. Whether these lesions were benign or malignant is not known. Technetium Tc99m Sestamibi uptake can occur in both benign and malignant disease. THE CLINICAL USEFULNESS OF A POSITIVE Technetium Tc99m Sestamibi IMAGE IN THE ABSENCE OF AN ABNORMAL MAMMOGRAM OR A PALPABLE LESION IS NOT KNOWN.

16. HOW SUPPLIED/STORAGE AND HANDLING

Kit for the Preparation of Technetium Tc99m Sestamibi Injection is supplied as a 10 mL vial in kits of five (5) (NDC # 69945-092-20) or a carton of thirty (30) (NDC # 69945-092-40), sterile and non-pyrogenic.

The patient dose should be measured by a suitable radioactivity calibration system immediately prior to patient administration. Radiochemical purity should be checked prior to patient administration.

Parenteral drug products should be inspected visually for particulate matter and discoloration prior to administration whenever solution and container permit.

Prior to lyophilization the pH is between 5.6-5.7. The contents of the vial are lyophilized and stored under nitrogen. Store at 15-25°C (59-77°F) before and after reconstitution. Protect from light prior to reconstitution.
Technetium Tc99m Sestamibi contains no preservatives. Included in each five (5) vial kit is one (1) package insert and five (5) radioassay information labels with radiation warning symbol. Included in each thirty (30) vial carton is one (1) package insert and thirty (30) radioassay information labels with radiation warning symbol.

This reagent kit is approved by the U.S. Nuclear Regulatory Commission for distribution to persons licensed to use by-product material identified in §35.200 to 10 CFR Part 35, to persons who have a similar authorization issued by an Agreement State, and, outside the United States, to persons authorized by the appropriate authority.

17. PATIENT COUNSELING INFORMATION

CARDIOLITE® and MIRALUMA® are different names for the same drug (Kit for the Preparation of Technetium Tc99m Sestamibi Injection). Patients should be advised to inform their health care provider if they had an allergic reaction to either drug or if they had an imaging study with either drug.

Lactation: Interruption of breastfeeding after exposure of Technetium Tc99m Sestamibi is not necessary, however, a lactating woman should be advised to consider the restricting close contact with her breast fed infant to a maximum 5 hours in the 24 hour period after Technetium Tc99m Sestamibi administration in order to minimize radiation exposure [see Use in Specific Populations (8.2)].

©2022 Curium US LLC. Curium™ and the Curium logo are trademarks of a Curium company.

CARDIOLITE®, MIRALUMA® and Recon-o-Stat™ are trademarks of Lantheus Medical Imaging, Inc.

A092I3

Manufactured by:
Curium US LLC
2703 Wagner Place
Maryland Heights, MO 63043

Made in USA

CURIUM™

Package Label - Principal Display Panel - Vial Label

Kit for the Preparation of Technetium Tc 99m Sestamibi Injection
FOR INTRAVENOUS USE AFTER LABELING WITH ADDITIVE-FREE TECHNETIUM Tc 99m
See package insert for full prescribing information.
Rx only
Each sterile and non-pyrogenic vial contains: Tetrakis (2-methoxy isobutyl isonitrile) Copper (I) tetrafluoroborate-1 mg; Stannous Chloride Dihydrate-0.075 mg; L-Cysteine Hydrochloride Monohydrate-1 mg; Sodium Citrate Dihydrate-2.6 mg; Mannitol-20 mg. The pH is adjusted to 5.6 to 5.7 with HCl or NaOH prior to lyophilization. Sealed under nitrogen.
Store at 15° to 25°C (59° to 77°F). Protect from light.
Manufactured by:
Curium US LLC
Maryland Heights, MO 63043

Made in USA

CURIUM™
A092V3

R12/2018